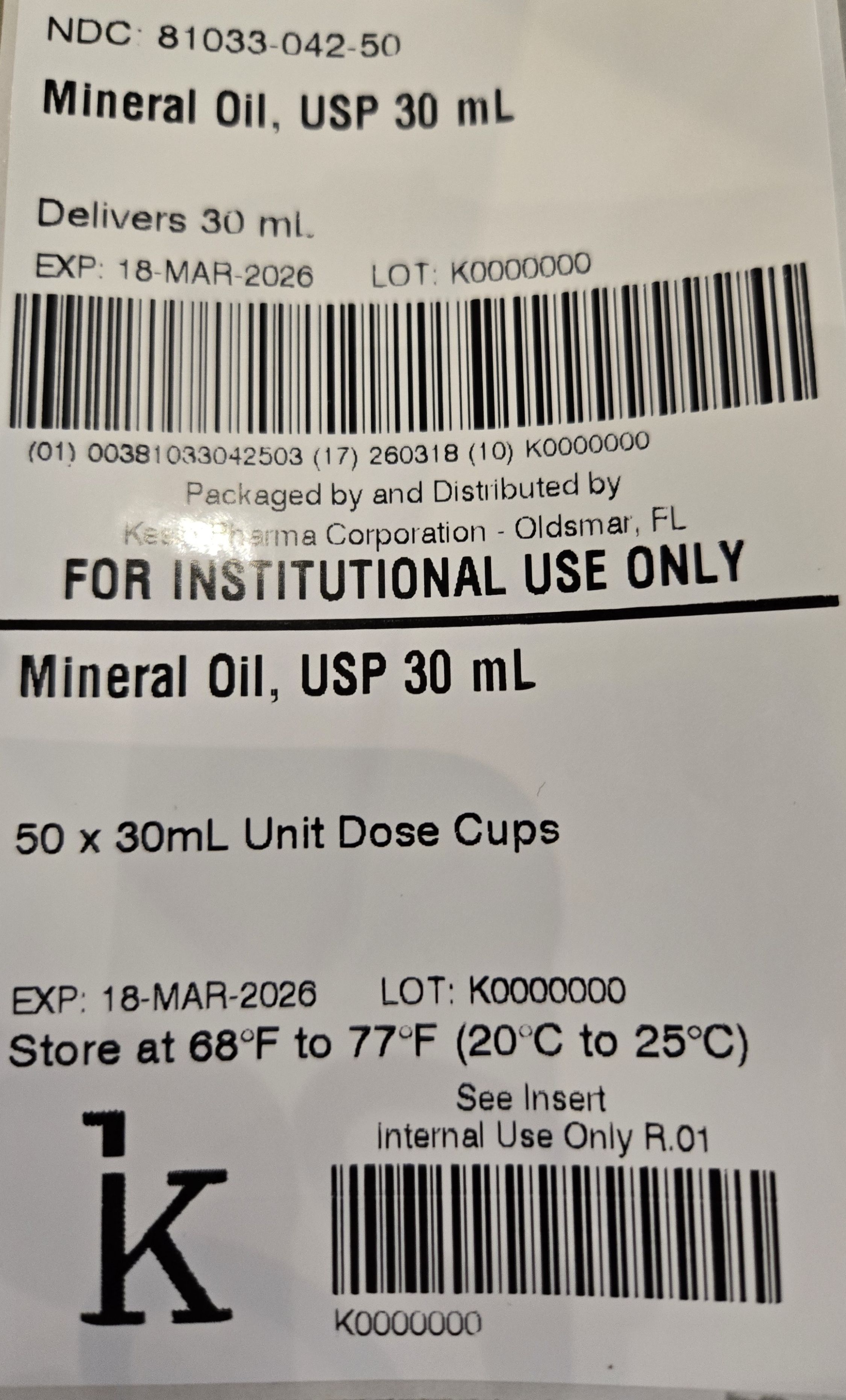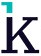 DRUG LABEL: Mineral Oil
NDC: 81033-042 | Form: SOLUTION
Manufacturer: Kesin Pharma Corporation
Category: otc | Type: HUMAN OTC DRUG LABEL
Date: 20250318

ACTIVE INGREDIENTS: MINERAL OIL 1000 mg/1 mL

Mineral Oil, USP 30 mL

Drug Facts

Active Ingredient

Mineral Oil (100%)

Lubricant Laxative

There are no other inactive ingredients.

Purpose

Lubricant Laxative

Uses

- relieves occasional constipation (irregularity)
- generally produces bowel movement in 6 to 8 hours

Warnings

Do not use

- if you have difficulty swallowing
- in children under 6 years of age
- if you are pregnant
- for a period longer than 1 week
- if you are bedridden or aged

Ask a doctor before use if you have

- abdominal pain, nausea, or vomiting
- noticed a sudden change in bowel habits that persists over a period of 2 weeks

Ask a doctor or pharmacist before use if you are

- presently taking a stool softener laxative
- taking any other drug. Take this product 2 or more hours before or after other drugs. Laxatives may affect how other drugs work.

When using

When using this product

- do not take with meals
- take only at bedtime

Stop use and ask a doctor if you have rectal bleeding or failure to have a bowel movement after use. These
could be signs of a serious condition.

If pregnant or breastfeeding, ask a health professional before use.

Keep out of reach of children. In case of overdose, get medical help or contact a Poison Control Center right away.

Directions

- do not take with meals
- take only at bedtime
- may be taken as a single dose or as directed by a doctor

Age | Dose
adults and children 12 years of age and over | 1 to 3 Tablespoons (15 mL to 45 mL) maximum 3 Tablespoons (45 mL) in 24 hours
children 6 to under 12 years of age | 1 to 3 teaspoons (5 mL to 15 mL) maximum 3 teaspoons (15 mL) in 24 hours
children under 6 years | do not use. consult a doctor.

Other information

- store at 20°C to 25°C (68°F to 77°F)
- protect from direct light
- NDC 81033-042-30: 30 mL unit dose cup
- NDC 81033-042-50: Carton containing 50 - 30 mL unit dose cups

Questions or comments ?

Call 1-833-537-4679

Packaged by:
Kesin Pharma
Oldsmar, FL 34677

Rev. 03/2025

PACKAGE LABEL

NDC 81033-042-50

Mineral Oil, USP 30 mL

Delivers 30 mL

FOR INSTITUTIONAL ONLY

50 x 30 mL Unit Dose Cups

Store at 68ºF to 77ºF (20ºC to 25ºC)